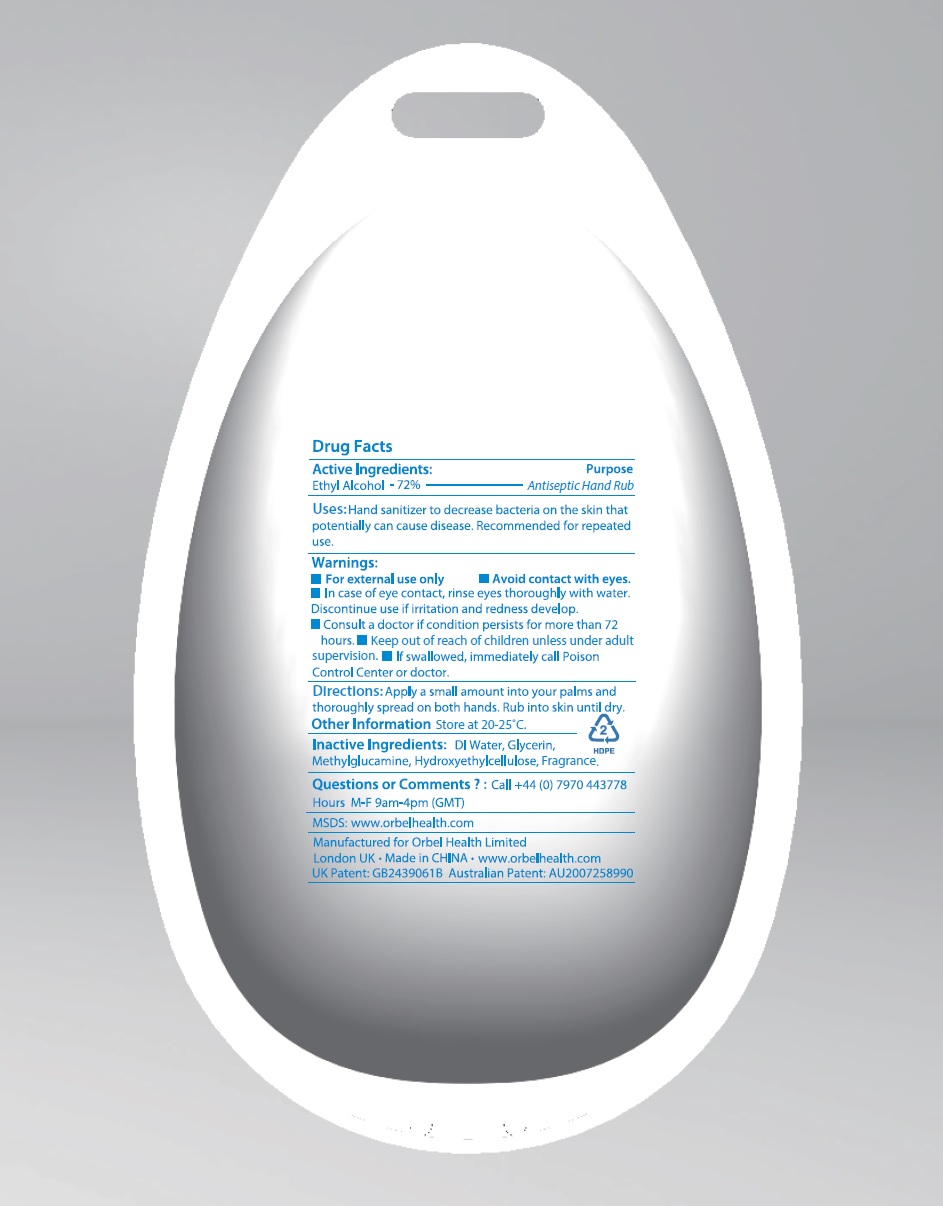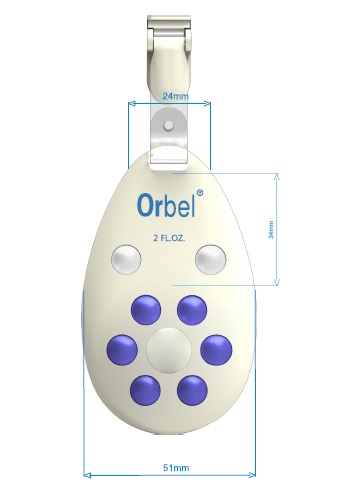 DRUG LABEL: Orbel
NDC: 61805-090 | Form: LIQUID
Manufacturer: Bath Concept Cosmetics (Dongguan) Co., Ltd
Category: otc | Type: HUMAN OTC DRUG LABEL
Date: 20190508

ACTIVE INGREDIENTS: ALCOHOL 72 mL/100 mL
INACTIVE INGREDIENTS: WATER; GLYCERIN; MEGLUMINE; HYDROXYETHYL CELLULOSE (4000 MPA.S AT 1%); BUTYLPHENYL METHYLPROPIONAL; ISOMETHYL-.ALPHA.-IONONE; .ALPHA.-AMYLCINNAMALDEHYDE; .ALPHA.-AMYLCINNAMYL ALCOHOL; BENZYL ALCOHOL; BENZYL BENZOATE; CITRAL; .BETA.-CITRONELLOL, (+/-)-; COUMARIN; EUGENOL; GERANIOL; .ALPHA.-HEXYLCINNAMALDEHYDE; HYDROXYISOHEXYL 3-CYCLOHEXENE CARBOXALDEHYDE; HYDROXYCITRONELLAL; LIMONENE, (+)-; LINALOOL, (+/-)-; EVERNIA PRUNASTRI; PSEUDEVERNIA FURFURACEA

Orbel

Active Ingredient

Ethyl Alcohol-72%

Purpose

Antiseptic Hand Rub

Uses

Hand sanitizer to decrease bacteria on the skin that potentially can cause disease. Recommended for repeated use.

Warnings

For external use only

Avoid contact with eyes.

In case of eye contact, rinse eyes thoroughly with water. Discontinue use if irritation and redness develop.

Consult a doctor if condition persists for more than 72 hours.

Keep out of reach of children unless under adult supervision.

If swallowed, immediately call Poison Control Center or doctor.

Directions

- Apply small amount into your palm and thoroughly spread on both hands. Rub into skin until dry.

Questions or Comments ? :

Call +44 (0) 7970 443778

Hours M-F 9am-4pm (GMT)

Other Information

- Store at 20-25°C

Inactive ingredients

DI water, Glycerin, Methylglucamine, Hydroxyethylcellulose, Fragrance

Principal Display Panel

Orbel

Ethyl Alcohol 72%